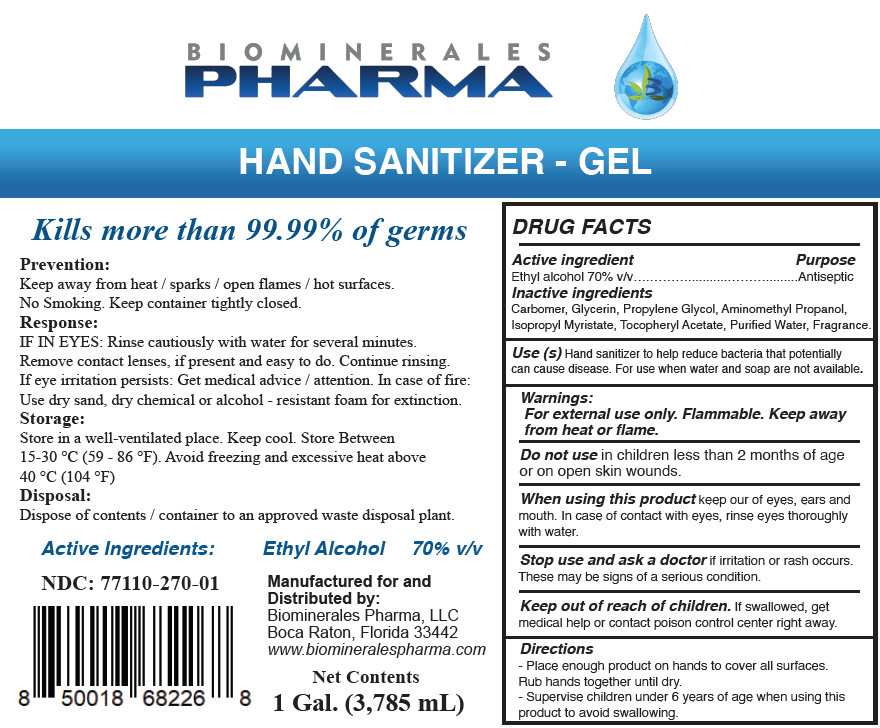 DRUG LABEL: HAND SANITIZER
NDC: 77110-270 | Form: GEL
Manufacturer: Biominerales Pharma, LLC
Category: otc | Type: HUMAN OTC DRUG LABEL
Date: 20200611

ACTIVE INGREDIENTS: Alcohol 70 mL/100 mL
INACTIVE INGREDIENTS: CARBOMER HOMOPOLYMER, UNSPECIFIED TYPE; GLYCERIN; PROPYLENE GLYCOL; AMINOMETHYLPROPANOL; ISOPROPYL MYRISTATE; .ALPHA.-TOCOPHEROL ACETATE; WATER

HAND SANITIZER

DRUG FACTS

Active ingredient

Ethyl alcohol 70% v/v

Purpose

Antiseptic

Inactive ingredients

Carbomer, Glycerin, Propylene Glycol, Aminomethyl Propanol, Isopropyl Myristate, Tocopheryl Acetate, Purified Water, Fragrance.

Use (s)

Hand sanitizer to help reduce bacteria that potentially can cause disease. For use when water and soap are not available.

Warnings

For external use only. Flammable. Keep away from heat or flame.

Do not use in children less than 2 months of age or on open skin wounds.

When using this product keep our of eyes, ears and mouth. In case of contact with eyes, rinse eyes thoroughly with water.

Stop use and ask a doctor if irritation or rash occurs. These may be signs of a serious condition.

Keep out of reach of children. If swallowed, get medical help or contact poison control center right away.

Directions

- Place enough product on hands to cover all surfaces. Rub hands together until dry.
- Supervise children under 6 years of age when using this product to avoid swallowing.

Manufactured for and
Distributed by:
Biominerales Pharma, LLC
Boca Raton, Florida 33442

PRINCIPAL DISPLAY PANEL - 3,785 mL Bottle Label

BIOMINERALES
PHARMA

HAND SANITIZER - GEL

Kills more than 99.99% of germs

Prevention:
Keep away from heat / sparks / open flames / hot surfaces.
No Smoking. Keep container tightly closed.
Response:
IF IN EYES: Rinse cautiously with water for several minutes.
Remove contact lenses, if present and easy to do. Continue rinsing.
If eye irritation persists: Get medical advice / attention. In case of fire:
Use dry sand, dry chemical or alcohol - resistant foam for extinction.
Storage:
Store in a well-ventilated place. Keep cool. Store Between
15-30 °C (59 - 86 °F). Avoid freezing and excessive heat above
40 °C (104 °F)
Disposal:
Dispose of contents / container to an approved waste disposal plant.

Active Ingredients: Ethyl Alcohol 70% v/v

NDC: 77110-270-01

Manufactured for and
Distributed by:
Biominerales Pharma, LLC
Boca Raton, Florida 33442
www.biomineralespharma.com

Net Contents
1 Gal. (3,785 mL)